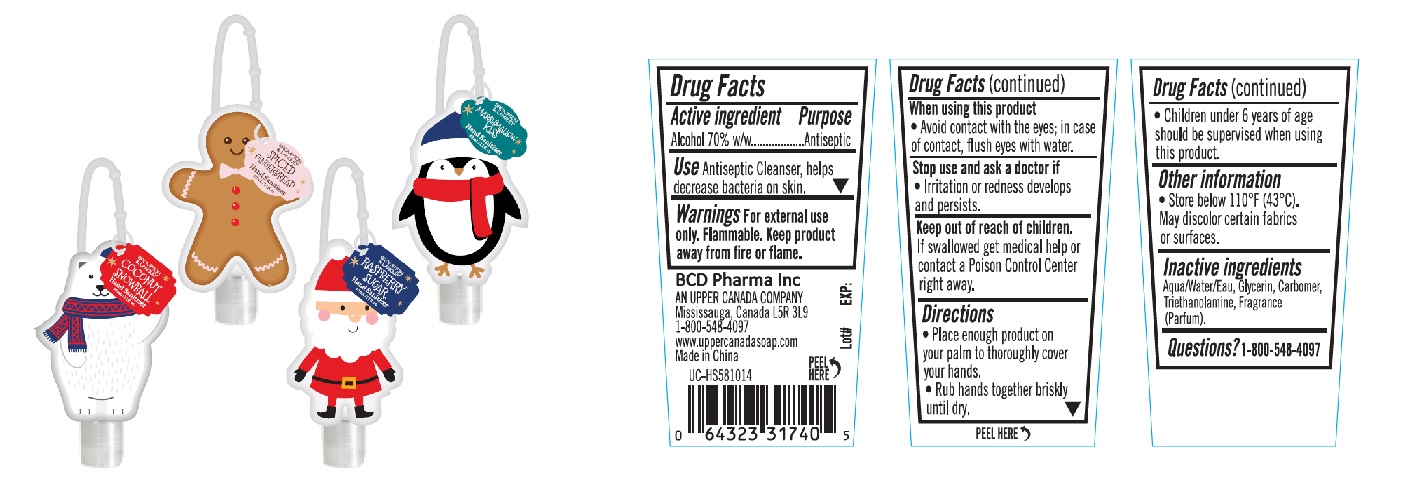 DRUG LABEL: Brompton and Langley Hand Sanitizer
NDC: 77607-005 | Form: GEL
Manufacturer: Xiamen Afgamarine Biotechnology Co., Ltd.
Category: otc | Type: HUMAN OTC DRUG LABEL
Date: 20211008

ACTIVE INGREDIENTS: ALCOHOL 700 mg/1 mL
INACTIVE INGREDIENTS: WATER; GLYCERIN; CARBOMER 934; TROLAMINE

Drug Facts

Active ingredient

Alcohol 70% w/w

Purpose

Antiseptic

Use

Antiseptic Cleanser, helps decrease bacteria on skin.

Warnings

For external use only. Flammable. Keep product away from fire or flame.

When using this product

Avoid contact with the eyes; in case of contct, flush eyes with water.

Stop use and ask a doctor if

Irritation or redness develops and persists.

Keep out of reach of children.

If swallowed, get medical help or contact a Poison Control Center right away.

Directions

- Place enough product on your palm to thoroughly cover your hands.
- Rub hands together briskly until dry.
- Children under 6 years of age should be supervised when using this product.

Other information

- Store below 110°F (43°C). May discolor certain fabrics or surfaces.

Inactive ingredients

Aqua/Water/Eau, Glycerin, Carbomer, Triethanolamine, Fragrance (Parfum).

Questions?

1-800-548-4097